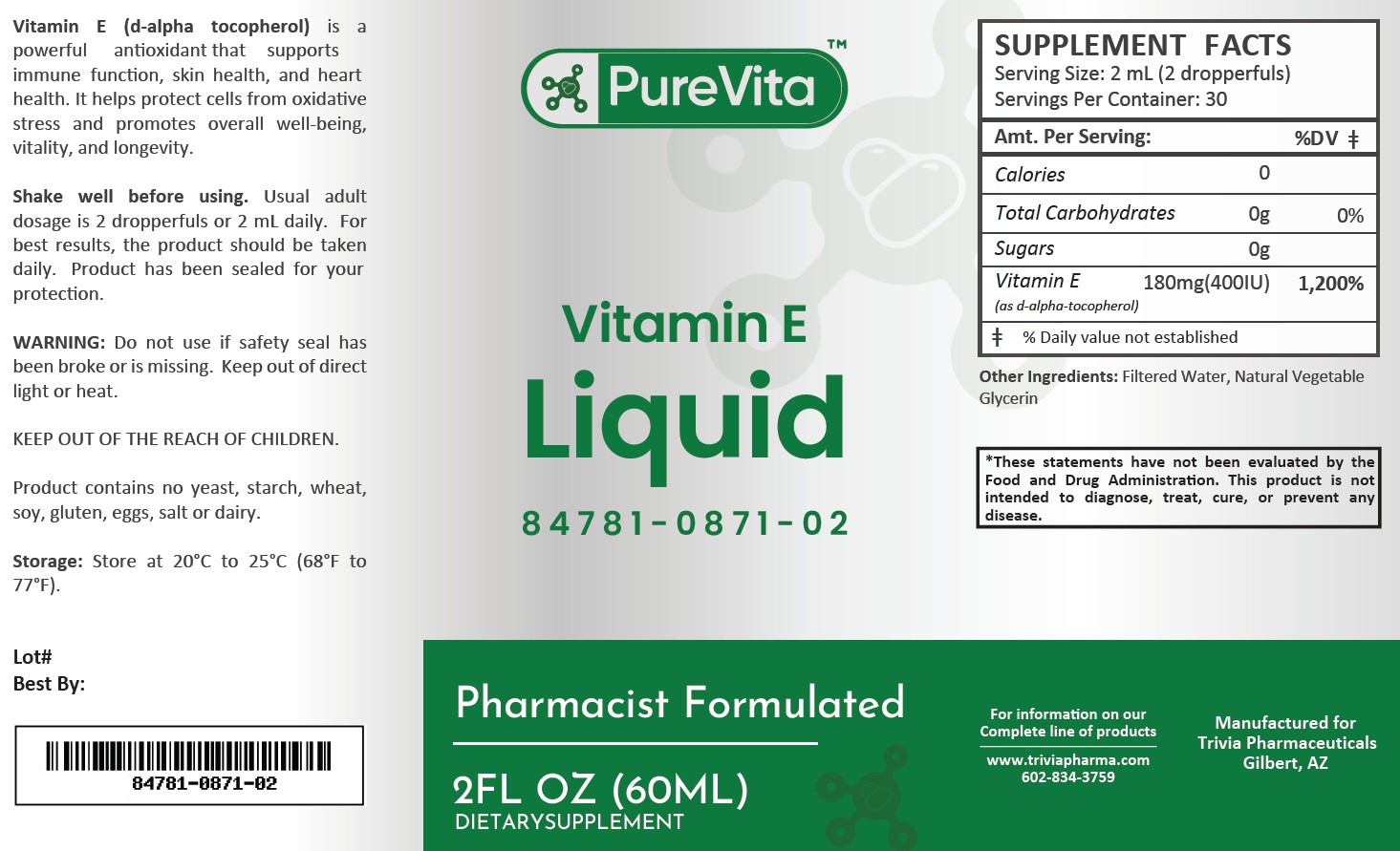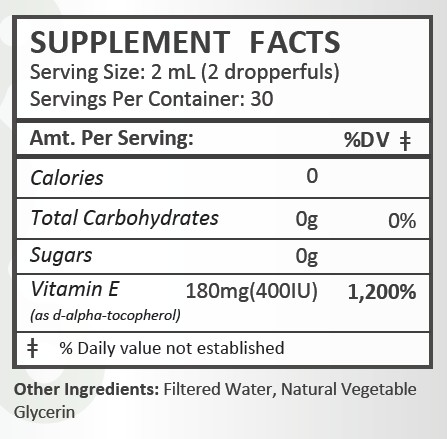 DRUG LABEL: PureVita Vitamin E
NDC: 84781-871 | Form: LIQUID
Manufacturer: Trivia Pharmaceuticals, LLC
Category: other | Type: Dietary Supplement
Date: 20250306

ACTIVE INGREDIENTS: .ALPHA.-TOCOPHEROL, D- 180 mg/2 mL

PureVita Vitamin E

Health Claim:

PureVita Vitamin E Liquid

Description:

PureVita Vitamin E (d-alpha-tocopherol) is a powerful antioxidant that supports immune function, skin health and heart health. It helps protect cells from oxidative stress and promotes overall well-being, vitality and longevity.

This listed product is not a National Drug Code, but instead has merely been formatted to comply with standard industry practice for pharmacy and insurance computer systems.

Warnings:

Do not use if safety seal has been broken or is missing. Keep out of direct light or heat.

KEEP OUT OF THE REACH OF CHILDREN.

Product contains no yeast, starch, wheat, soy, gluten, eggs, salt or dairy.

Dosage and Administration:

Usual adult dose is 2 dropperfuls or 2 mL daily. For the best results, the product should be taken daily. Product has been sealed for your protection.

How Supplied:

PureVita Vitamin E Liquid is supplied as white, clear liquid.

84781-0871-02

Reserved for Professional Recommendation: All prescriptions using this product shall be pursuant to state statutes as applicable. This is not an Orange Book product. There are no implied or explicit claims on therapeutic equivalence.

Manufactured for:

Trivia Pharmaceuticals

Gilbert, AZ

Storage:

Storage: Store at 20oC to 25oC (68oF to 77oF). Keep refrigerated after opening.